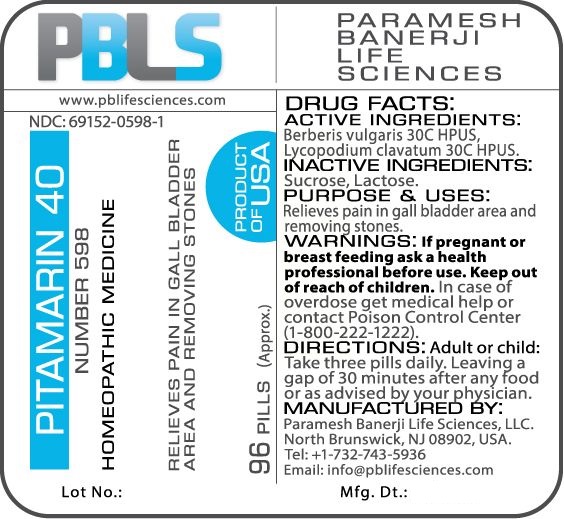 DRUG LABEL: Pitamarin 40 (Number 598)
NDC: 69152-0598 | Form: PELLET
Manufacturer: Paramesh Banerji Life Sciences LLC
Category: homeopathic | Type: HUMAN OTC DRUG LABEL
Date: 20170323

ACTIVE INGREDIENTS: LYCOPODIUM CLAVATUM SPORE 30 [hp_C]/1 1; BERBERIS VULGARIS ROOT BARK 30 [hp_C]/1 1
INACTIVE INGREDIENTS: SUCROSE; LACTOSE

DRUG FACTS: Active Ingredients

Berberis vulgaris 30C HPUS, Lycopodium clavatum 30C HPUS

Inactive Ingredients

Sucrose, Lactose

Purpose

Relieves pain in gall bladder area and removing stones

Uses

Relieves pain in gall bladder area and removing stones

Warnings

If pregnant or breast feeding ask a health professional before use.

Keep out of reach of children. In case of overdose, get medical help or contact a Poison Control Center (1-800-222-1222) right away.

Direction

Adult or child: Take three pills daily. Leaving a gap of 30 minutes after any food or as advised by your physician.

Manufactured by

Paramesh Banerji Life Sciences, LLC.

North Brunswick, NJ 08902, USA.

Tel: +1-732-743-5936

Email: info@pblifesciences.com

Principal Display Panel

NDC: 69152-0598-1

Pitamarin 40

Number 598

Homeopathic Medicine

Relieves pain in gall bladder area and removing stones

96 Pills (Approx.)

Product of USA